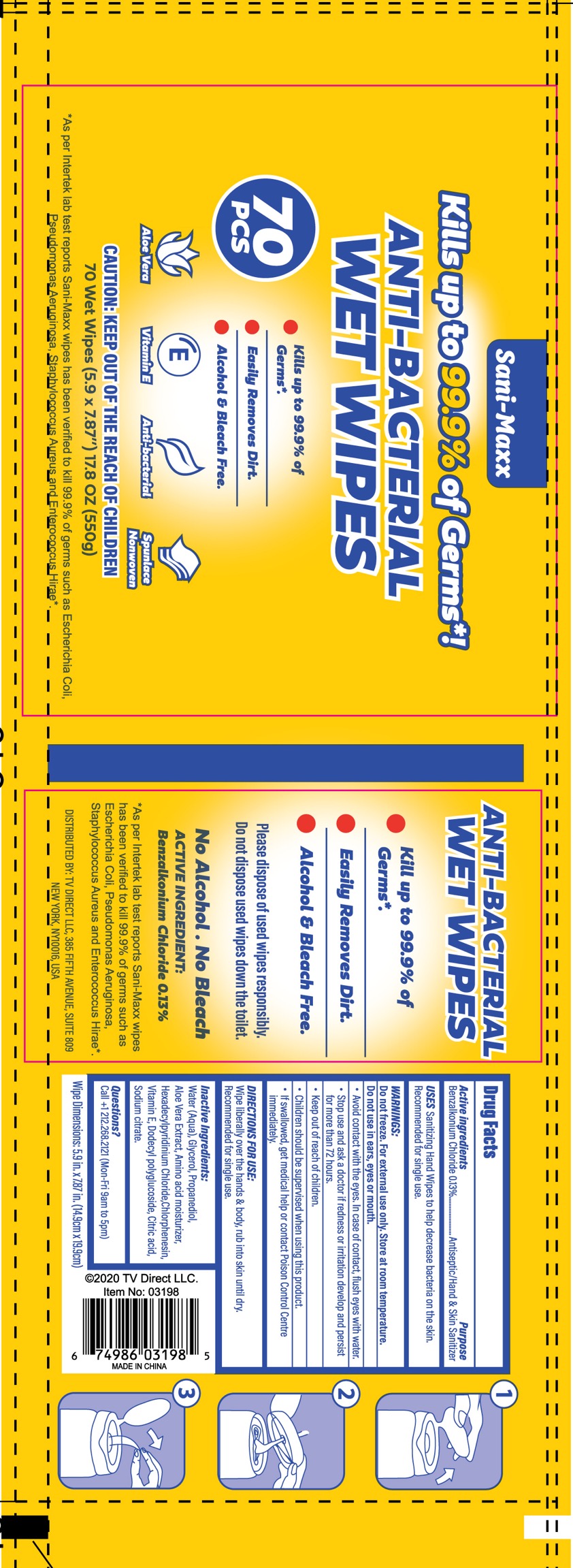 DRUG LABEL: WET WIPES
NDC: 78055-010 | Form: PATCH
Manufacturer: Dalian Oupai Technology Co.,Ltd.
Category: otc | Type: HUMAN OTC DRUG LABEL
Date: 20201010

ACTIVE INGREDIENTS: BENZALKONIUM CHLORIDE 0.13 g/100 g
INACTIVE INGREDIENTS: GLYCERIN 0.5 g/100 g; WATER 98.73 g/100 g; PROPANEDIOL 0.2 g/100 g; ALOE VERA LEAF 0.1 g/100 g; BETAINE 0.1 g/100 g; CETYLPYRIDINIUM CHLORIDE ANHYDROUS 0.05 g/100 g; CHLORPHENESIN 0.05 g/100 g; .ALPHA.-TOCOPHEROL 0.05 g/100 g; POLY(LAURYLGLUCOSIDE)-7 0.05 g/100 g; CITRIC ACID  MONOHYDRATE 0.02 g/100 g; SODIUM CITRATE 0.02 g/100 g

Active Ingredients

Benzalkonium Chloride 0.13% . Purpose: Antiseptic/Hand & Skin Sanitizer

Do not use in ears,eyes or mouth.

WHEN USING

USES Sanitizing Hand Wipes to help decrease bacteria on the skin.Recommended for single use.

Stop use and ask a doctor if redness or irritation develop and persist for more than 72 hours.

Keep out of reach of children.

If swallowed, get medical help or contact Poison Control Centre immediately.

DIRECTIONS FOR USE:

Wipe liberally over the hands & body,rub into skin until dry.

Recommended for single use.

Inactive ingredients

Water(Aqua),Glycerol,Propanediol,Aloe Vera Extract, Amino acid moisturizer,Hexadecylpyridinium Chloride,Chlorphenesin,Vitamin E,Dodecyl polyglucoside,Citric acid,Sodium citrate.

Purpose

Antiseptic/hand & Skin sanitizer

USES

USES Sanitizing Hand Wipes to help decrease bacteria on the skin.Recommeded for single use.

WARNING

Do not freeze.For external use only,Store at room temperature.

Do not use in ears,eyes or mouth.

Avoid contact with the eyes.In case of contact,flush eyes with water.

Stop use and ask a doctor if redness or irritation develop and persist for more than 72 hours.

Keep out of reach of children.

Children should be supervised when using this product.

If swallowed, get medical help or contact Poison Control Centre immediately.